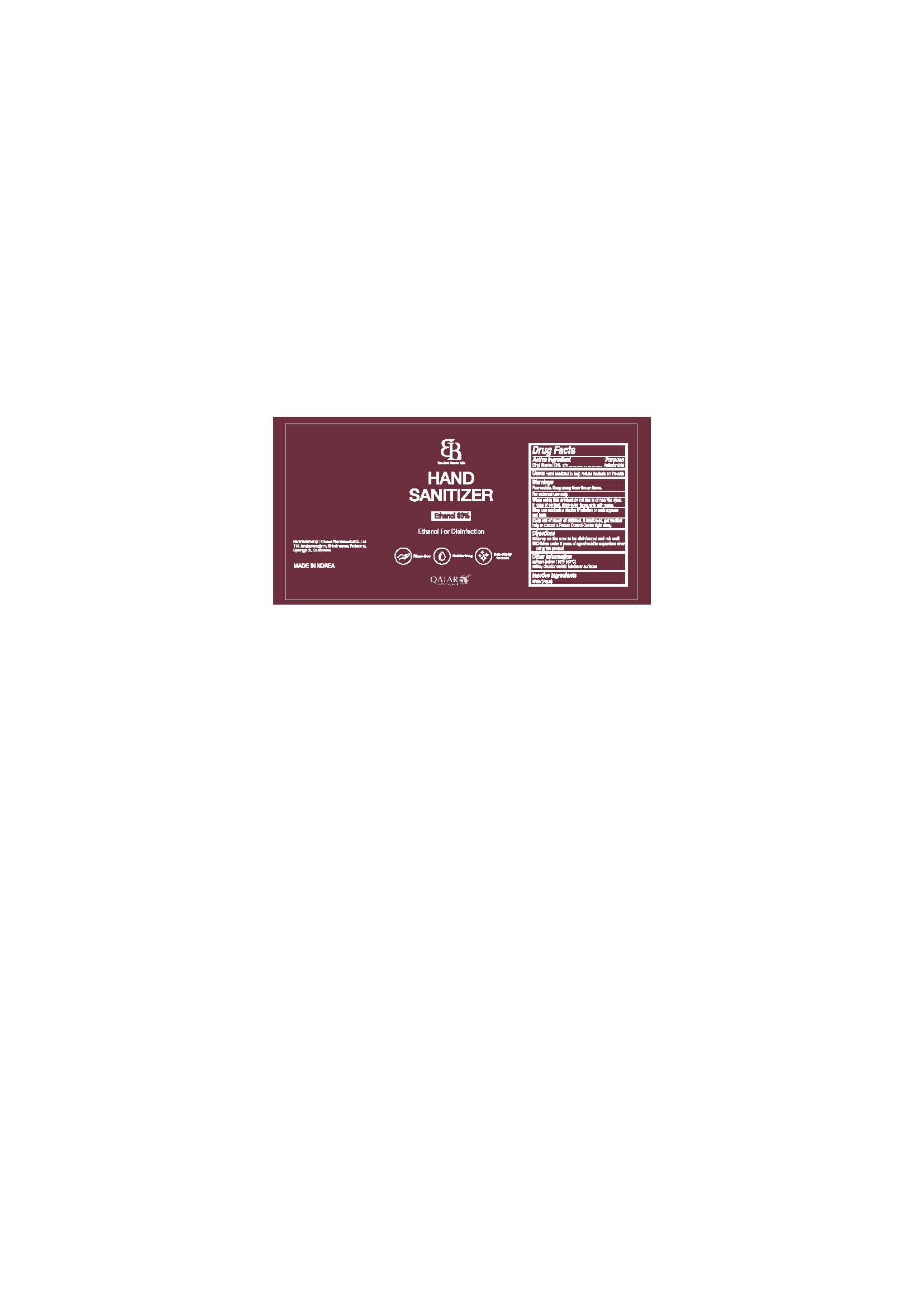 DRUG LABEL: K.Doctor Clean Ethanol for Disinfection
NDC: 74724-0004 | Form: LIQUID
Manufacturer: K.Boeun Pharmaceutical Co.,Ltd.
Category: otc | Type: HUMAN OTC DRUG LABEL
Date: 20210224

ACTIVE INGREDIENTS: ALCOHOL 83 g/100 mL
INACTIVE INGREDIENTS: WATER

Drug Facts

ACTIVE INGREDIENT

Ethanol (95%)

INACTIVE INGREDIENT

Water

PURPOSE

Antiseptic

KEEP OUT OF REACH OF THE CHILDREN

INDICATIONS AND USAGE

Store under 30°C (86°F)

WARNINGS

For external use only.

Flammable, keep away from fire or flame.

When using this product keep out of eyes. If contact with eyes occurs, rinse promptly and thoroughly with water.

Stop use and ask a doctor if significant irritation or sensitization develops.

Keep out of reach of children. If swallowed, get medical help or contact a Poison Control Center right away.

DOSAGE AND ADMINISTRATION

Spray on the area to be disinfected and rub well

Children under 6 years of age should be supervised when using this product